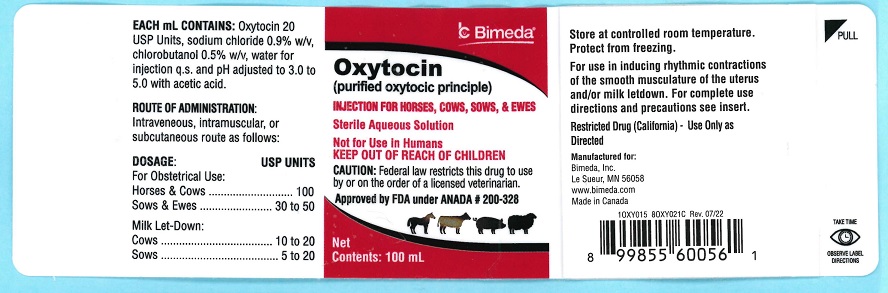 DRUG LABEL: Oxytocin
NDC: 61133-6013 | Form: INJECTION, SOLUTION
Manufacturer: Bimeda, Inc.
Category: animal | Type: PRESCRIPTION ANIMAL DRUG LABEL
Date: 20231213

ACTIVE INGREDIENTS: OXYTOCIN 20 [USP'U]/1 mL

DESCRIPTION

Oxytocin

(purified oxytocic principle)
INJECTION FOR HORSES, COWS, SOWS, & EWES

20 USP Units per mL

HAZARDOUS
Not for Use in Humans
KEEP OUT OF REACH OF CHILDREN

CAUTION: Federal law restricts this drug to use by or on the order of a licensed veterinarian.

DESCRIPTION: Oxytocin injection is a sterile aqueous solution of highly purified oxytocic principle derived by synthesis or obtained from the posterior lobe of the pituitary gland of healthy domestic animals used for food by humans. Oxytocin injection contains 20 USP Units of Oxytocin and less than 0.4 units of presser activity per mL. Each mL of sterile solution also contains 0.9% w/v sodium chloride, 0.5% w/v chlorobutanol (as a preservative), with water for injection q.s. and pH adjusted to 3.0 to 5.0 with acetic acid.

ACTIONS: Oxytocin acts directly on the smooth musculature of the uterus in all species to induce rhythmic contractions, although in some species the uterine cervix does not respond to oxytocin. The responsiveness of the uterine musculature to oxytocin varies greatly with the stage of the reproductive cycle. During the early phases of pregnancy the uterus is relatively insensitive to the effects of oxytocin, while in the late phases the sensitivity is markedly increased. Most authorities attribute this varying response to the varying levels of estrogen and progesterone during the course of pregnancy. Oxytocin also has been shown to exert a milk ejecting effect, occasionally referred to as the galactogogic effect. The actual mechanism by which oxytocin stimulates the release of milk from the mammary glands is not know with certainty, but oxytocin is presumed to act on certain smooth muscle elements in the gland.

INDICATIONS AND USAGE

INDICATIONS: Because of the specific action of oxytocin upon the uterine musculature, it is recommended as an aid in the management of the following conditions:

1. To precipitate labor.2. To accelerate normal parturition.3. Postpartum evacuation of uterine debris.4. Postoperative contraction of the uterus following a cesarean section and control of uterine hemorrhage.

Oxytocin will contract the smooth muscle cells of the mammary gland to induce milk let-down if the udder is in a proper physiological state.

CONTRAINDICATIONS

CONTRAINDICATION: Do not use in dystocia due to abnormal presentation of the fetus until correction is accomplished.

PRECAUTIONS

PRECAUTIONS: Oxytocin is a potent preparation, accordingly, it should be administered with due caution. For prepartum usage full dilation of the cervix should be accomplished either naturally or through the administration of estrogen prior to oxytocin therapy.

DOSAGE AND ADMINISTRATION:

Obstetrical Use: Inject aseptically by the intravenous, intramuscular or subcutaneous route as follows:

Ewes, Sows:

1.5 to 2.5mL......................30 to 50 USP Units

Cows, Horses:

5.0mL...............................100 USP Units

These dosages are recommended, and may be repeated as indicated.

Milk Let-down:

Inject aseptically by the intravenous, intramuscular or subcutaneous route

Cows:

0.5 to 1.0mL.....................10 to 20 USP Units

Sows:

0.25 to 1.0mL....................5 to 20 USP Units

These dosages are recommended and may be repeated as necessary.

Note: Oxytocin will not induce milk let-down unless the udder is in proper physiological state.

ADVERSE REACTIONS

To report suspected adverse drug events, for technical assistance or to obtain a copy of the Safety Data Sheet (SDS), contact Bimeda, Inc. at 1-888-524-6332. For additional information about adverse drug experience reporting for animal drugs, contact FDA at 1-888-FDA-VETS or online at www.fda.gov/reportanimalae.

HOW SUPPLIED: 100mL multiple dose vials.

Approved by FDA under ANADA # 200-328

STORAGE AND HANDLING

Store at controlled room temperature. Protect from freezing.